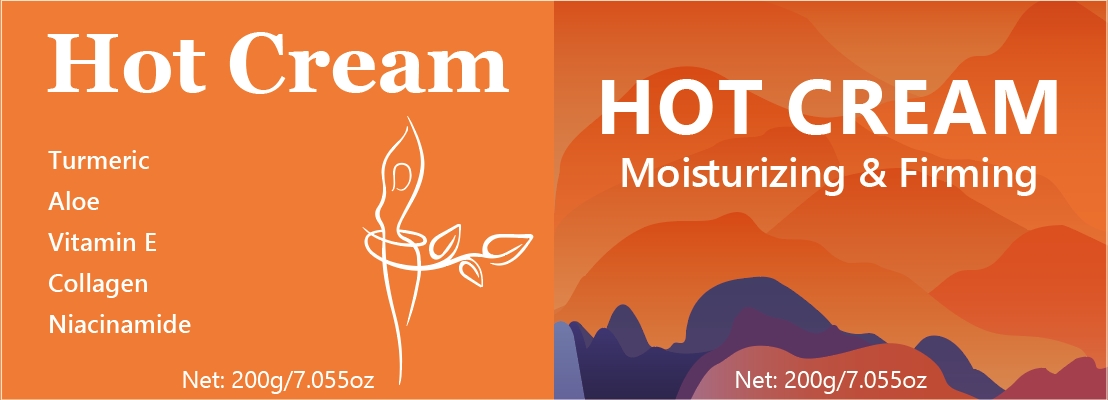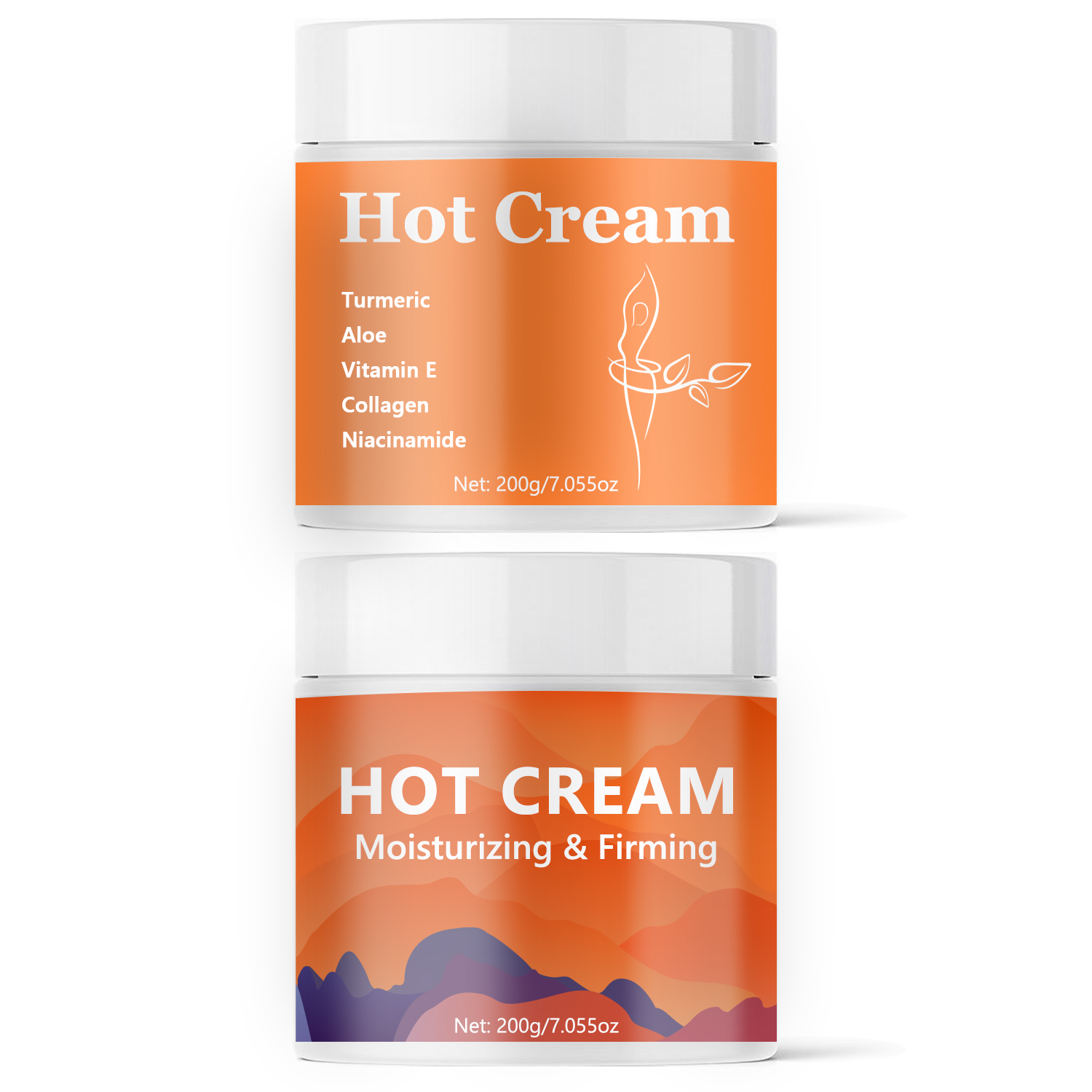 DRUG LABEL: Hot Cream
NDC: 84025-207 | Form: CREAM
Manufacturer: Guangzhou Yanxi Biotechnology Co., Ltd
Category: otc | Type: HUMAN OTC DRUG LABEL
Date: 20241011

ACTIVE INGREDIENTS: ISOPROPYL PALMITATE 3 mg/100 mL; GLYCERIN 5 mg/100 mL
INACTIVE INGREDIENTS: WATER

DOSAGE AND ADMINISTRATION

use as sport body cream

WARNINGS

keep out of children

INACTIVE INGREDIENT

Aqua

INDICATIONS AND USAGE

for daliy sport body care

Keep out of children

PURPOSE

Helps tighten muscles during exercise